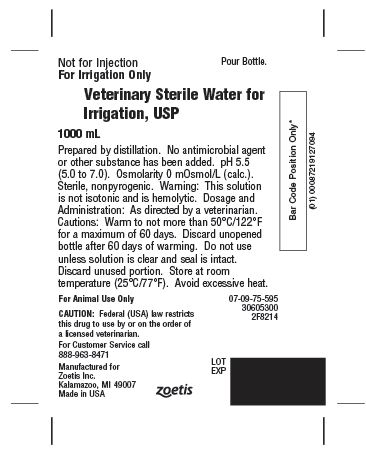 DRUG LABEL: Veterinary Sterile Water
NDC: 54771-4942 | Form: IRRIGANT
Manufacturer: Zoetis Inc.
Category: animal | Type: PRESCRIPTION ANIMAL DRUG LABEL
Date: 20160809

ACTIVE INGREDIENTS: WATER 1 mL/1 mL

Veterinary Sterile Water for Irrigation, USP

Description

Prepared by distillation. No antimicrobial agent or other substance has been added. pH 5.5 (5.0 to 7.0). Osmolarity 0 mOsmol / L (calc.). Sterile, nonpyrogenic.

Warning:

This solution is not isotonic and is hemolytic.

Dosage and Administration

As directed by a veterinarian.
Cautions: Warm to not more than 50ºC / 122ºF for a maximum of 60 days. Discard unopened bottle after 60 days of warming. Do not use unless solution is clear and seal is intact. Discard unused portion.

Storage:

Store at room temperature (25ºC / 77ºF). Avoid excessive heat.

For Animal Use Only

CAUTION:

Federal law (USA) restricts this drug to use by or on the order of a licensed veterinarian.

For Customer Service call 888-963-8471

Manufactured for

Zoetis Inc.

Kalamazoo, MI 49007

Made in USA

PRINCIPAL DISPLAY PANEL

Veterinary Sterile Water for

Irrigation, USP

Not for Injection Pour Bottle.

For Irrigation Only

1000 mL

Zoetis
Veterinary Sterile Water